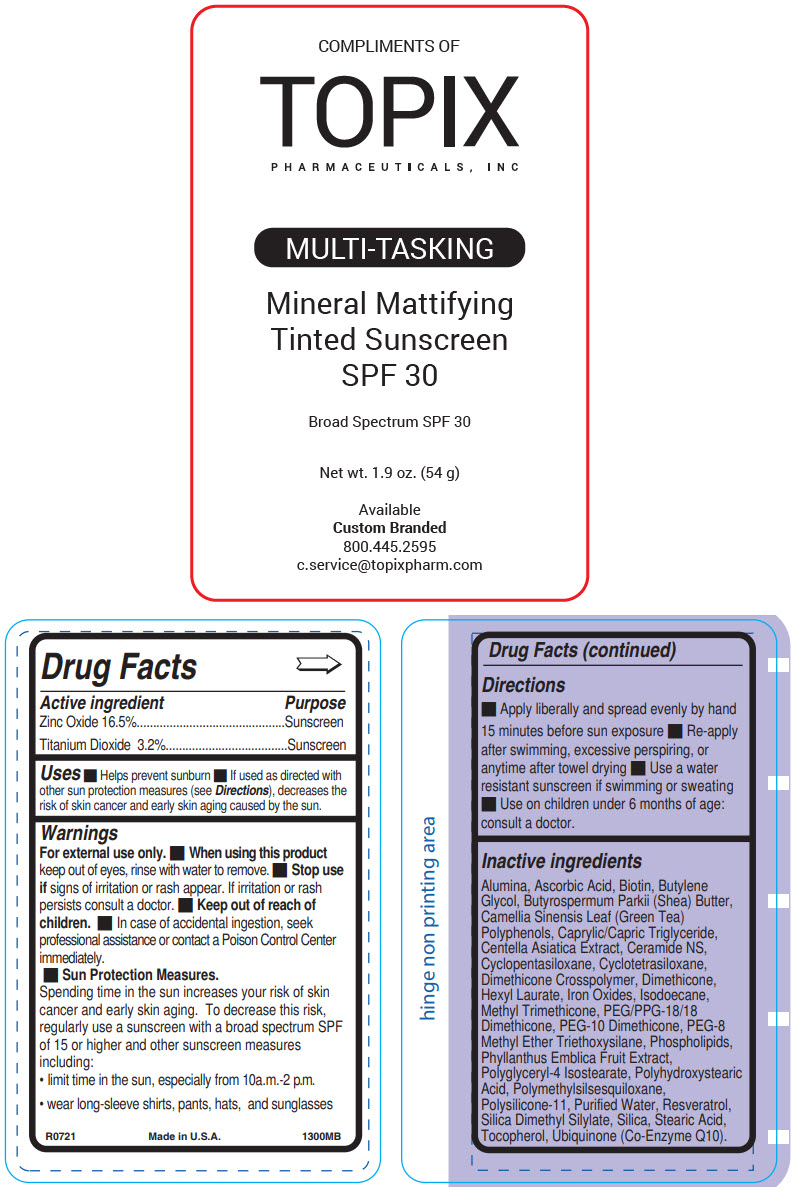 DRUG LABEL: Topix Mineral Mattifying Tinted Sunscreen 
NDC: 51326-130 | Form: CREAM
Manufacturer: Topiderm, Inc.
Category: otc | Type: HUMAN OTC DRUG LABEL
Date: 20230224

ACTIVE INGREDIENTS: ZINC OXIDE 162 mg/1 g; TITANIUM DIOXIDE 32 mg/1 g
INACTIVE INGREDIENTS: ALUMINUM OXIDE; ASCORBIC ACID; BIOTIN; BUTYLENE GLYCOL; SHEA BUTTER; GREEN TEA LEAF; MEDIUM-CHAIN TRIGLYCERIDES; CENTELLA ASIATICA WHOLE; CERAMIDE NG; CYCLOMETHICONE 5; CYCLOMETHICONE 4; DIMETHICONE CROSSPOLYMER (450000 MPA.S AT 12% IN CYCLOPENTASILOXANE); DIMETHICONE; HEXYL LAURATE; FERROUS OXIDE; ISODODECANE; METHYL TRIMETHICONE; PEG/PPG-18/18 DIMETHICONE; PEG-10 DIMETHICONE (220 CST); OMEGA-3 FATTY ACIDS; PHYLLANTHUS EMBLICA FRUIT; POLYGLYCERYL-4 ISOSTEARATE; POLYHYDROXYSTEARIC ACID (2300 MW); POLYMETHYLSILSESQUIOXANE (11 MICRONS); DIMETHICONE/VINYL DIMETHICONE CROSSPOLYMER (SOFT PARTICLE); WATER; RESVERATROL; SILICA DIMETHYL SILYLATE; SILICON DIOXIDE; STEARIC ACID; .ALPHA.-TOCOPHEROL; COENZYME Q10, (2Z)-

Topix Mineral Mattifying Tinted Sunscreen
SPF 30

Drug Facts

ACTIVE INGREDIENT

Active ingredient | Purpose
Zinc Oxide 16.5% | Sunscreen
Titanium Dioxide 3.2% | Sunscreen

Uses

- Helps prevent sunburn
- If used as directed with other sun protection measures (see Directions), decreases the risk of skin cancer and early skin aging caused by the sun.

Warnings

For external use only.

- When using this product keep out of eyes, rinse with water to remove.

- Stop use if signs of irritation or rash appear. If irritation or rash persists consult a doctor.

- Keep out of reach of children.

- In case of accidental ingestion, seek professional assistance or contact a Poison Control Center immediately.

- Sun Protection Measures.
  Spending time in the sun increases your risk of skin cancer and early skin aging. To decrease this risk, regularly use a sunscreen with a broad spectrum SPF of 15 or higher and other sunscreen measures including:
  - limit time in the sun, especially from 10a.m.-2 p.m.
  - wear long-sleeve shirts, pants, hats, and sunglasses

Directions

- Apply liberally and spread evenly by hand 15 minutes before sun exposure
- Re-apply after swimming, excessive perspiring, or anytime after towel drying
- Use a water resistant sunscreen if swimming or sweating
- Use on children under 6 months of age: consult a doctor.

Inactive ingredients

Alumina, Ascorbic Acid, Biotin, Butylene Glycol, Butyrospermum Parkii (Shea) Butter, Camellia Sinensis Leaf (Green Tea) Polyphenols, Caprylic/Capric Triglyceride, Centella Asiatica Extract, Ceramide NS, Cyclopentasiloxane, Cyclotetrasiloxane, Dimethicone Crosspolymer, Dimethicone, Hexyl Laurate, Iron Oxides, Isodoecane, Methyl Trimethicone, PEG/PPG-18/18 Dimethicone, PEG-10 Dimethicone, PEG-8 Methyl Ether Triethoxysilane, Phospholipids, Phyllanthus Emblica Fruit Extract, Polyglyceryl-4 Isostearate, Polyhydroxystearic Acid, Polymethylsilsesquiloxane, Polysilicone-11, Purified Water, Resveratrol, Silica Dimethyl Silylate, Silica, Stearic Acid, Tocopherol, Ubiquinone (Co-Enzyme Q10).

PRINCIPAL DISPLAY PANEL - 54 g Bottle Label

COMPLIMENTS OF
TOPIX
PHARMACEUTICALS, INC

MULTI-TASKING

Mineral Mattifying
Tinted Sunscreen
SPF 30

Broad Spectrum SPF 30

Net wt. 1.9 oz. (54 g)

Available
Custom Branded
800.445.2595
c.service@topixpharm.com